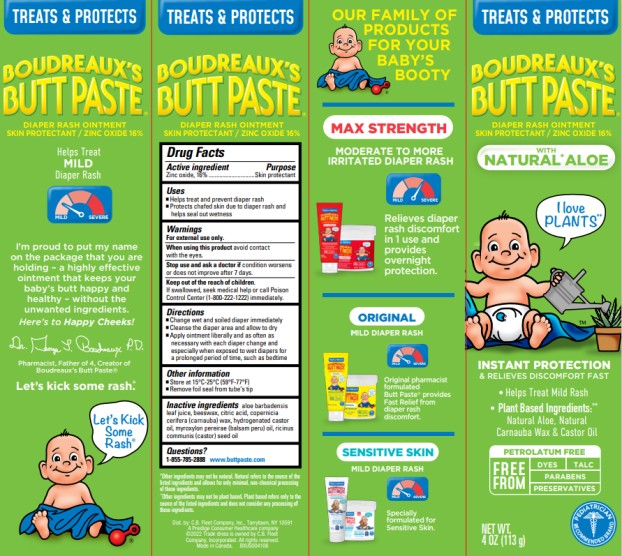 DRUG LABEL: Boudreauxs
NDC: 0132-0334 | Form: CREAM
Manufacturer: C.B. Fleet Company, Inc.
Category: otc | Type: HUMAN OTC DRUG LABEL
Date: 20251023

ACTIVE INGREDIENTS: ZINC OXIDE 16 g/113 g
INACTIVE INGREDIENTS: ALOE BARBADENSIS LEAF JUICE; BEESWAX; CITRIC ACID; CARNAUBA WAX; HYDROGENATED CASTOR OIL; BALSAM PERU; CASTOR OIL

Boudreauxs Butt Paste Natural 0132-0334

Drug Facts

Active Ingredient

Zinc Oxide, 16%

Purpose

Skin Protectant

Uses

- Helps treat and prevent diaper rash
- Protects chafed skin due to diaper rash and helps seal out wetness

Warnings

For external use only

When using this product

avoid contact with the eyes

Stop use and ask a doctor

if condition worsens or does not improve after 7 days

Keep out of the reach of children

If swallowed, seek medical help or call Poison Control Center (1-800-222-1222) immediately

Directions for Use

- Change wet and soiled diaper immediately
- Cleanse the diaper area and allow to dry
- Apply ointment liberally and as often as necessary with each diaper change and especially when exposed to wet diapers for prolonged period of time, such as bedtime

Other Information

- Store at room temperature, 15C-25C (59F-77F)
- Remove foil seal from the tube's tip

Inactive Ingredients

aloe barbadensis leaf juice, beeswax, citric acid, copernicia cerifera (carnauba) wax, hydrogenated castor oil, myroxylon pereirae (balsam peru) oil, ricinus communis (castor) seed oil

Questions?

1-855-785-2888 www.buttpaste.com

Principal Display Panel

TREATS & PROTECTS

BOUDREAUX’S
BUTT PASTE

DIAPER RASH OINTMENT
SKIN PROTECTANT/ ZINC OXIDE 16%

WITH NATURAL* ALOE

NET WT.
4OZ (113 g)